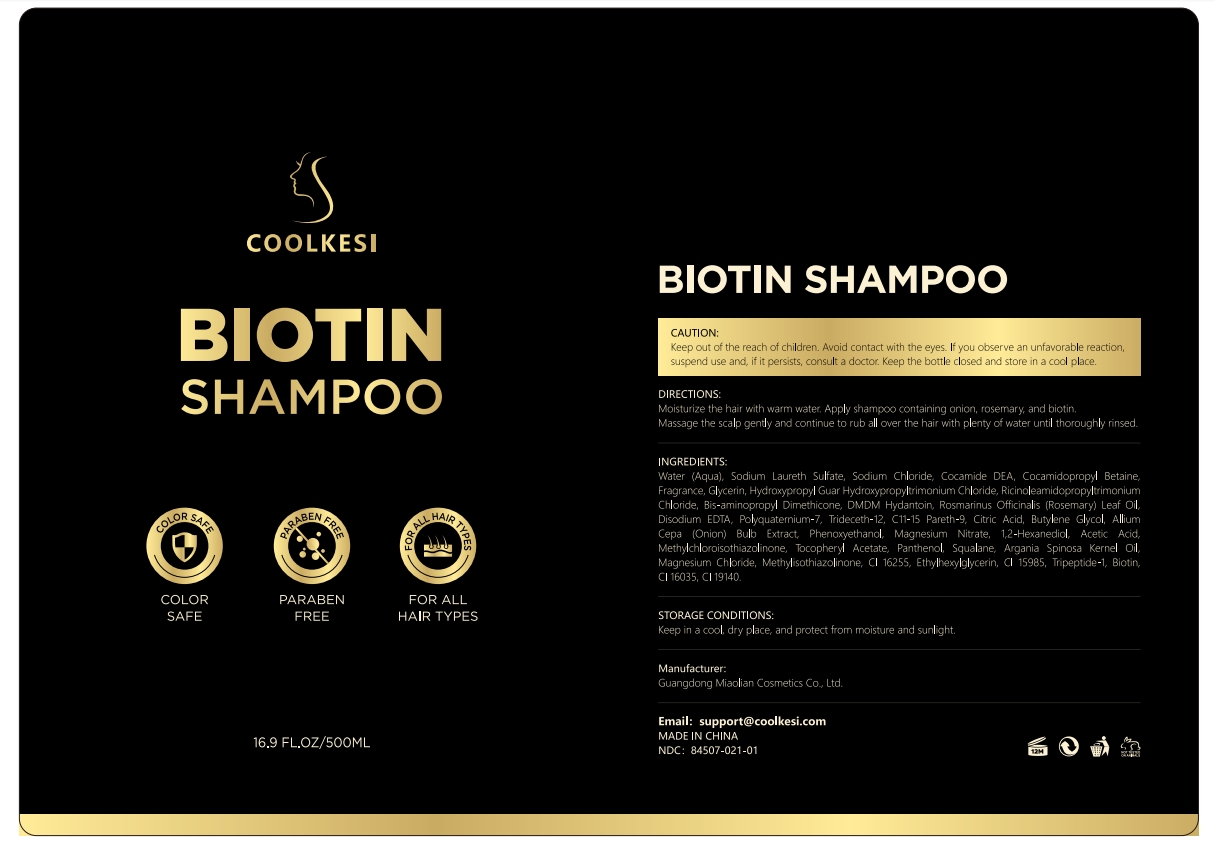 DRUG LABEL: COOLKESI BOTIN SHAM-POO
NDC: 84507-039 | Form: SHAMPOO
Manufacturer: Guangdong Miaolian Cosmetics Co., Ltd.
Category: otc | Type: HUMAN OTC DRUG LABEL
Date: 20250610

ACTIVE INGREDIENTS: ROSMARINUS OFFICINALIS (ROSEMARY) LEAF OIL 0.1 mg/100 mL; MELALEUCA ALTERNIFOLIA (TEA TREE) LEAF OIL 0.1 mg/100 mL; ROSA DAMASCENA FLOWER OIL 0.1 mg/100 mL
INACTIVE INGREDIENTS: BIOTIN; EDETATE DISODIUM; PAEONIA ALBIFLORA FLOWER; GLYCOL DISTEARATE; COCAMIDE MEA; AMPELOPSIS JAPONICA ROOT; SODIUM CARBONATE; PANAX GINSENG WHOLE; ETHYLHEXYLGLYCERIN; ATRACTYLODES MACROCEPHALA ROOT; WOLFIPORIA COCOS WHOLE; POLYQUATERNIUM-10 (125 MPA.S AT 2%); C11-15 PARETH-9; AMMONIUM LAURYL SULFATE; GLYCERIN; AMODIMETHICONE (240 CST); ALOE BARBADENSIS LEAF; MENTHOL; PANAX GINSENG ROOT; WATER; SODIUM LAURETH SULFATE; SODIUM COCOAMPHOACETATE; MORINDA CITRIFOLIA SEED OIL; LAURETH-3; TRIDECETH-12; ETHANOLAMINE; ACETIC ACID; TREMELLA FUCIFORMIS WHOLE; COCAMIDOPROPYL BETAINE; ACRYLATES/C10-30 ALKYL ACRYLATE CROSSPOLYMER (60000 MPA.S); DIMETHICONOL (40 CST); COCAMIDE DEA; FRAGRANCE 13576; SODIUM LAUROYL SARCOSINATE; GUAR HYDROXYPROPYLTRIMONIUM CHLORIDE; HYDROLYZED WHEAT PROTEIN (ENZYMATIC, 3000 MW); POLYQUATERNIUM-7; SODIUM HYDROXIDE; PLATYCLADUS ORIENTALIS LEAF; ZINGIBER OFFICINALE (GINGER) ROOT OIL; ALLANTOIN; BUTYROSPERMUM PARKII (SHEA) BUTTER; COCOS NUCIFERA (COCONUT) OIL; BUTYLENE GLYCOL; GLYCOL STEARATE; PHENOXYETHANOL

DOSAGE AND ADMINISTRATION

Moisturize the hair with warm water. Apply shampoo containing onion, rosemary, and biotin.Massage the scalp gently and continue to rub all over the hair with plenty of water until thoroughly rinsed.

WARNINGS

Keep in a cool, dry place, and protect from moisture and sunlight.

INACTIVE INGREDIENT

WATER
SODIUM LAURETH SULFATE
AMMONIUM LAURYL SULFATE
DIMETHICONOL
COCAMIDE DEA
GLYCOL DISTEARATE
COCAMIDE MEA
COCAMIDOPROPYL BETAINE
FRAGRANCE
ACRYLATES/C10-30 ALKYL ACRYLATE CROSSPOLYMER
ALLANTOIN
GLYCERIN
SODIUM COCOAMPHOACETATE
SODIUM LAUROYL SARCOSINATE
BUTYLENE GLYCOL
GUAR HYDROXYPROPYLTRIMONIUM CHLORIDE
MORINDA CITRIFOLIA SEED OIL
BUTYROSPERMUM PARKII (SHEA) BUTTER
COCOS NUCIFERA (COCONUT) OIL
GLYCOL STEARATE
POLYQUATERNIUM-10
BIS-AMINOPROPYL DIMETHICONE
LAURETH-3
DISODIUM EDTA
HYDROLYZED WHEAT PROTEIN
POLYQUATERNIUM-7
SODIUM HYDROXIDE
PHENOXYETHANOL
C11-15 PARETH-9
TRIDECETH-12
BIOTIN
ALOE BARBADENSIS LEAF EXTRACT
PLATYCLADUS ORIENTALIS LEAF EXTRACT
ETHANOLAMINE
ETHYLHEXYLGLYCERIN
MENTHOL
MELALEUCA ALTERNIFOLIA (TEA TREE) LEAF OIL
ROSMARINUS OFFICINALIS (ROSEMARY) LEAF OIL
ROSA DAMASCENA FLOWER OIL
ACETIC ACID
SODIUM CARBONATE
PANAX GINSENG ROOT POWDER
AMPELOPSIS JAPONICA ROOT POWDER
ATRACTYLODES MACROCEPHALA ROOT POWDER
PORIA COCOS EXTRACT
PAEONIA ALBIFLORA ROOT EXTRACT
TREMELLA FUCIFORMIS (MUSHROOM) EXTRACT
BLETIA HYACINTHINA BULB EXTRACT
ZINGIBER OFFICINALE (GINGER) ROOT EXTRACT
PANAX GINSENG EXTRACT

INDICATIONS AND USAGE

Improves the scalp environment, repairs damaged hair, and moisturizes hair. This product contains plant essences to repair the scalp barrier, provide a non-greasy moisturizing effect, and make hair look full and natural.

KEEP OUT OF REACH OF CHILDREN

Keep out of the reach of children. Avoid contact with the eyes. If you observe an unfavorable reaction, suspend use and, if it persists, consult a doctor. Keep the bottle closed and store in a cool place.

PURPOSE

Improves the scalp environment, repairs damaged hair, and moisturizes hair.

ACTIVE INGREDIENT

MELALEUCA ALTERNIFOLIA (TEA TREE) LEAF OIL--------0.1%
ROSMARINUS OFFICINALIS (ROSEMARY) LEAF OIL--------0.1%
ROSA DAMASCENA FLOWER OIL--------0.1%